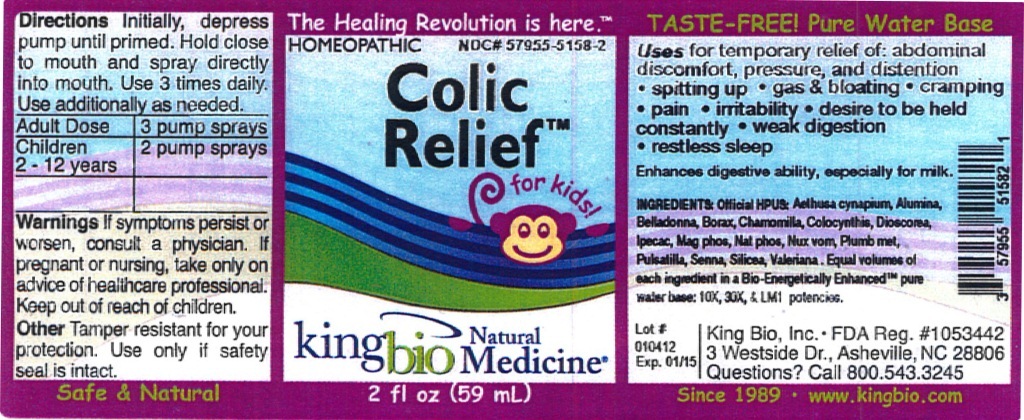 DRUG LABEL: Colic Relief
NDC: 57955-5158 | Form: LIQUID
Manufacturer: King Bio, Inc.
Category: homeopathic | Type: HUMAN OTC DRUG LABEL
Date: 20120330

ACTIVE INGREDIENTS: AETHUSA CYNAPIUM 10 [hp_X]/59 mL; ALUMINUM OXIDE 10 [hp_X]/59 mL; ATROPA BELLADONNA 10 [hp_X]/59 mL; SODIUM BORATE 10 [hp_X]/59 mL; MATRICARIA RECUTITA 10 [hp_X]/59 mL; DIOSCOREA VILLOSA TUBER 10 [hp_X]/59 mL; IPECAC 10 [hp_X]/59 mL; MAGNESIUM PHOSPHATE, DIBASIC TRIHYDRATE 10 [hp_X]/59 mL; SODIUM PHOSPHATE, DIBASIC, HEPTAHYDRATE 10 [hp_X]/59 mL; STRYCHNOS NUX-VOMICA SEED 10 [hp_X]/59 mL; LEAD 10 [hp_X]/59 mL; PULSATILLA VULGARIS 10 [hp_X]/59 mL; SENNA LEAF 10 [hp_X]/59 mL; SILICON DIOXIDE 10 [hp_X]/59 mL; VALERIAN 10 [hp_X]/59 mL
INACTIVE INGREDIENTS: WATER

Colic Relief

Active Ingredients

Official HPUS: Aethusa cynapium, Alumina, Belladonna, Borax, Chamomilla, Colocynthis, Dioscorea villosa, Ipecacuanha, Magnesia phosphorica, Natrum phosphoricum, Nux vomica, Plumbum metallicum, Pulsatilla, Senna, Silicea, Valeriana officinalis.

Reference image: colic relief.jpg

Inactive Ingredient

Equal volumes of each ingredient in a Bio-Energetically Enhanced pure water base: 10X, 30X, and LM1 potencies.

Reference image: colic relief.jpg

Purposes

Uses for temporary relief of:

- abdominal discomfort, pressure, and distention
- spitting up
- gas and bloating
- cramping
- pain
- irritability
- desire to be held constantly
- weak digestion
- restless sleep

Enhanced digestive ability, especially for milk.
Reference image: colic relief.jpg

Directions

Directions Initially depress pump until primed. Hold close to mouth and spray directly into mouth. Use 3 times daily. Use additionally as needed.

Adult dose - 3 pump sprays

Children 2-12 years - 2 pump sprays

Reference image: colic relief.jpg

Warnings

If symptoms persist or worsen, consult a physician. If pregnant or nursing, take only on advice of healthcare professional.

Other Tamper resistant for your protection. Use only if safely seal is intact.

Reference image: colic relief.jpg

Keep out of reach of children.

Reference image: colic relief.jpg

Uses

Uses for temporary relief of abdominal discomfort, pressure, and distention, spitting up, gas and bloating, cramping, pain, irritability, desire to be held constantly, weak digestion, restless sleep.

Enhances digestive ability, especially for milk.

Reference image: colic relief.jpg

PACKAGE LABEL

King Bio, Inc.

3 Westside Dr.

Asheville, NC 28806

Questions? Call 800.543.3245

www.kingbio.com

Reference image: colic relief.jpg